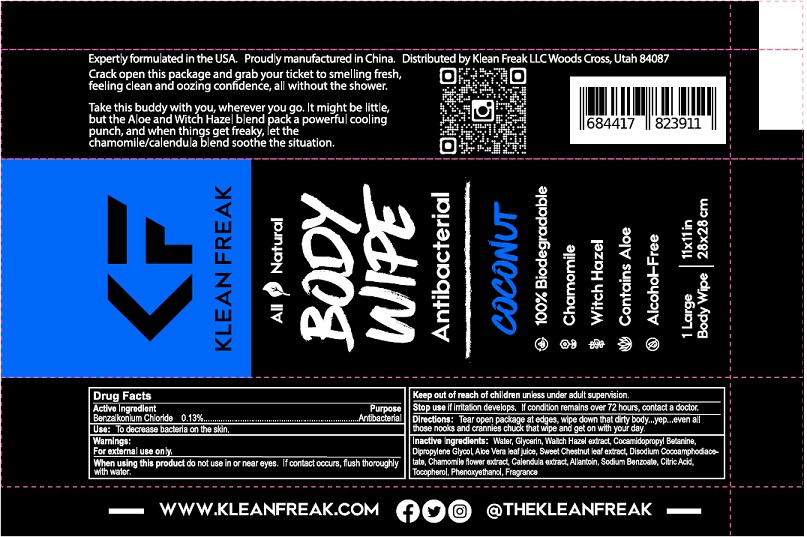 DRUG LABEL: Klean Freak
NDC: 78982-004 | Form: CLOTH
Manufacturer: KLEAN FREAK, LLC
Category: otc | Type: HUMAN OTC DRUG LABEL
Date: 20251128

ACTIVE INGREDIENTS: BENZALKONIUM CHLORIDE 0.13 g/100 g
INACTIVE INGREDIENTS: WATER; GLYCERIN; WITCH HAZEL; COCAMIDOPROPYL BETAINE; DIPROPYLENE GLYCOL; ALOE VERA LEAF; CASTANEA SATIVA LEAF; DISODIUM COCOAMPHODIACETATE; CHAMAEMELUM NOBILE FLOWER; CALENDULA ARVENSIS LEAF; ALLANTOIN; SODIUM BENZOATE; CITRIC ACID MONOHYDRATE; TOCOPHEROL; PHENOXYETHANOL

Active Ingredient

Benzalkonium Chloride 0.13% w/w.

Purpose

Antibacterial

Use

To decrease bacteria on the skin.

Warnings

For external use only.

When using this productdo not use in or near eyes. If contact occurs, flush thoroughly with water.

Stop useif irritation develops. If condition remains over 72 hours, contact a doctor.

KEEP OUT OF REACH OF CHILDREN

Keep out of reach of childrenunless under adult supervision.

Directions

Tear open package at edges, wipe down that dirty body ... yep ... even all those nooks and crannies chuck that wipe and get on with your day.

Inactive ingredients

Water, Glycerin, Waitch Hazel extract, Cocamidopropyl Betanine, Dipropylene Glycol, Aloe Vera leaf juice, Sweet Chestnut leaf extract, Disodium Cocoamphodiacetate, Chamomile flower extract, Calendula extract, Allantoin, Sodium Benzoate, Citric Acid, Tocopherol, Phenoxyethanol, Fragrance.